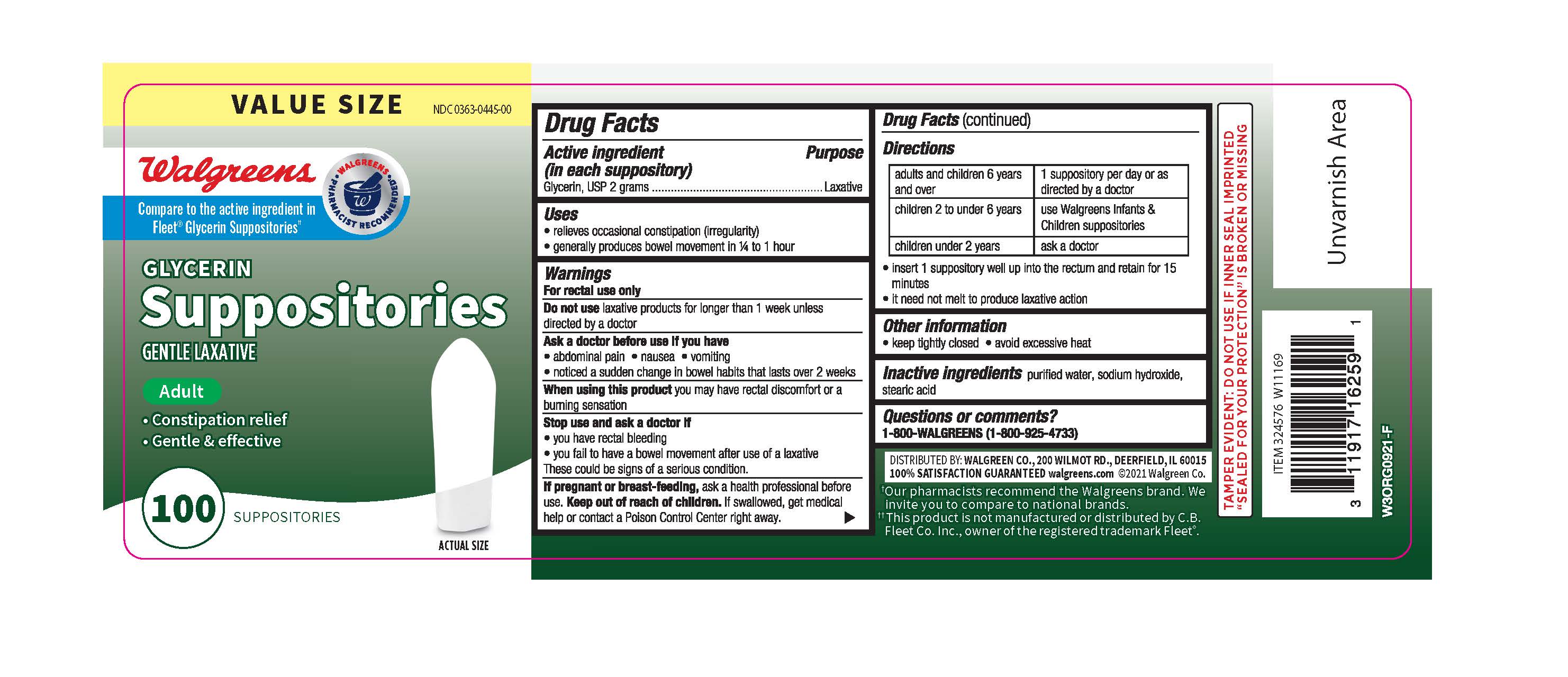 DRUG LABEL: Walgreens Adult Glycerin
NDC: 0363-0445 | Form: SUPPOSITORY
Manufacturer: Walgreens
Category: otc | Type: HUMAN OTC DRUG LABEL
Date: 20260115

ACTIVE INGREDIENTS: GLYCERIN 2 g/1 1
INACTIVE INGREDIENTS: STEARIC ACID; SODIUM HYDROXIDE; WATER

Walgreens®Glycerin Suppositories 100ct

Active Ingredient

Active Ingredient Purpose
(in each suppository)
Glycerin, USP 2 grams ............................................Laxative

Uses

-relieves occasional constipation (irregularity)

-generally produces bowel movement in 1/4 to 1 hour

Warnings

For rectal use only

Do not use laxative products for longer than 1 week unless directed by a doctor

Ask a doctor before use if you have

- abdominal pain - nausea - vomiting

- noticed a sudden change in bowel habits that lasts over 2 weeks

When using this product you may have rectal discomfort or a burning sensation

Stop use and ask a doctor if

-you have rectal bleeding

-you fail to have a bowel movement after use of a laxative

These could be signs of a serious condition.

If pregnant or breast-feeding, ask a health professional before use.

Keep out of reach of children.

If swallowed, get medical help or contact a Poison Control Center right away.

Directions

adults and children 6 years and over 1 suppository per day or as directed by a doctor
children 2 to under 6 years use Walgreens Infants & Children suppositories
children under 2 years ask a doctor

-Insert 1 suppository well up into the rectum and retain for 15 minutes
-It need not melt to produce laxative action

Other information

-keep tightly closed

-avoid excessive heat

Inactive ingredients

purified water, sodium hydroxide, stearic acid

Directions

adults and children 6 years and over 1 suppository per day or as directed by a doctor
children 2 to under 6 years use Walgreens Infants & Children suppositories
children under 2 years ask a doctor

-Insert 1 suppository well up into the rectum and retain for 15 minutes
-It need not melt to produce laxative action